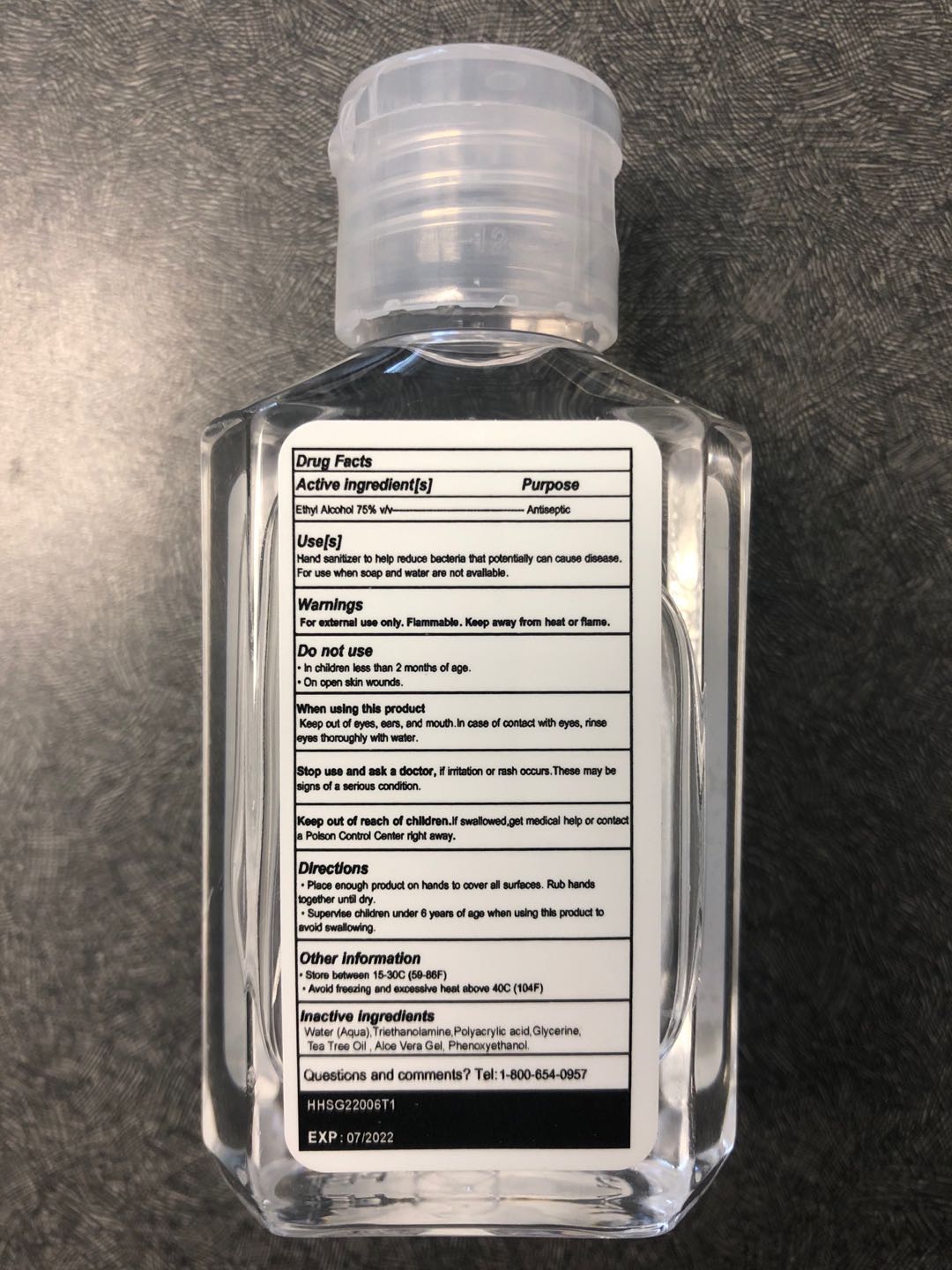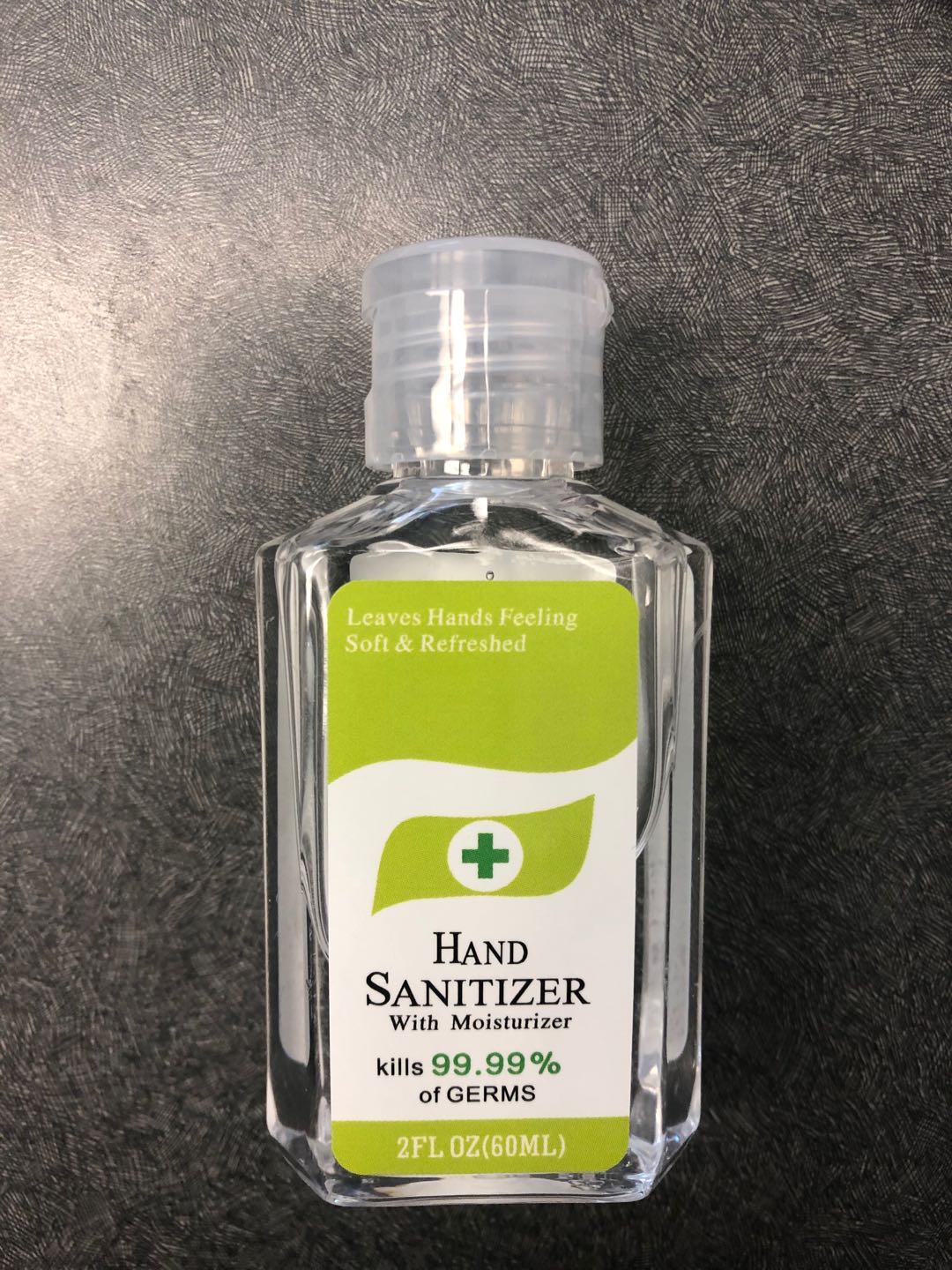 DRUG LABEL: Hand Sanitizer
NDC: 74496-8751 | Form: GEL
Manufacturer: Hans Manufacturer Inc.
Category: otc | Type: HUMAN OTC DRUG LABEL
Date: 20200815

ACTIVE INGREDIENTS: ALCOHOL 75 mL/100 mL
INACTIVE INGREDIENTS: TEA TREE OIL 0.05 mL/100 mL; PHENOXYETHANOL 0.2 mL/100 mL; GLYCERIN 0.89 mL/100 mL; TROLAMINE 0.39 mL/100 mL; WATER; ALOE VERA LEAF 0.1 mL/100 mL; POLYACRYLIC ACID (8000 MW) 0.35 mL/100 mL

Hand Sanitizer Gel 75% Alcohol

This is a hand sanitizer manufactured according to the Temporary Policy for Preparation of Certain Alcohol-Based Hand Sanitizer Products During the Public Health Emergency (CoViD-19); Guidance for Industry.

The hand sanitizer is manufactured using only the following ingredients in the preparation of the product (percentage in final product formulation):

1. Alcohol (ethanol) (USP or Food Chemical Codex (FCC) grade) (75%, volume/volume (v/v)) in an aqueous solution denatured according to Alcohol and Tobacco Tax and Trade Bureau regulations in 27 CFR part 20.
2. Glycerol (0.89% v/v).
3. Triethanolamine (0.39% v/v).
4. Polyacrylic acid (0.35% v/v).
5. Tea Tree Oil (0.05% v/v).
6. Aloe Vera Gel (0.1% v/v).
7. Phenoxyethanol (0.2% v/v).
8. Sterile distilled water or boiled cold water.

The firm does not add other active or inactive ingredients. Different or additional ingredients may impact the quality and potency of the product.

Active Ingredient(s)

Alcohol 75% v/v. Purpose: Antiseptic

Purpose

Antiseptic, Hand Sanitizer

Use

Hand Sanitizer to help reduce bacteria that potentially can cause disease. For use when soap and water are not available.

Warnings

For external use only. Flammable. Keep away from heat or flame

Do not use

- in children less than 2 months of age
- on open skin wounds

When using this product keep out of eyes, ears, and mouth. In case of contact with eyes, rinse eyes thoroughly with water.
Stop use and ask a doctor if irritation or rash occurs. These may be signs of a serious condition.
Keep out of reach of children. If swallowed, get medical help or contact a Poison Control Center right away.

Stop use and ask a doctor if irritation or rash occurs. These may be signs of a serious condition.

Keep out of reach of children. If swallowed, get medical help or contact a Poison Control Center right away.

Directions

- Place enough product on hands to cover all surfaces. Rub hands together until dry.
- Supervise children under 6 years of age when using this product to avoid swallowing.

Other information

- Store between 15-30C (59-86F)
- Avoid freezing and excessive heat above 40C (104F)

Inactive ingredients

Glycerin, Triethanolamine, Polyacrylic acid, Tea Tree Oil, Aloe Vera Gel, Phenoxyethanol, purified water USP

Package Label - Principal Display Panel

60 mL NDC: 74496-8751-1